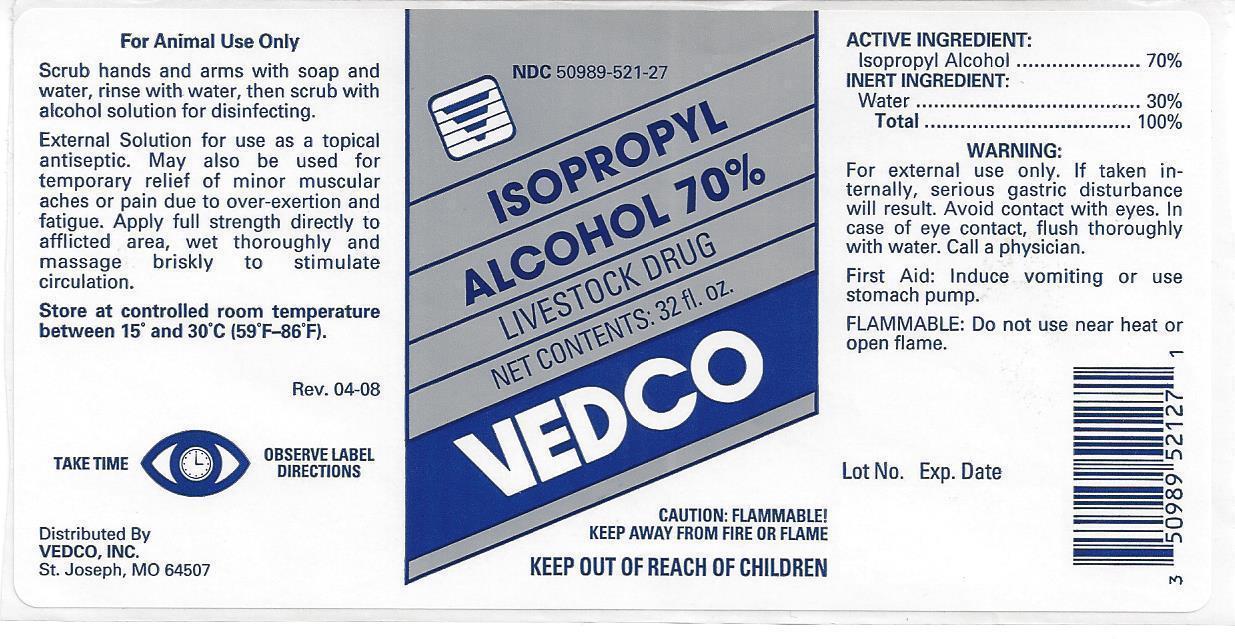 DRUG LABEL: Isopropyl Alcohol
NDC: 50989-521 | Form: LIQUID
Manufacturer: Vedco
Category: animal | Type: OTC ANIMAL DRUG LABEL
Date: 20131025

ACTIVE INGREDIENTS: ISOPROPYL ALCOHOL 70 mL/100 mL
INACTIVE INGREDIENTS: WATER

Isopropyl Alcohol 70%

NDC 50989-521-29 ISOPROPYL ALCOHOL 70% LIVESTOCK DRUG NET CONTENTS: 1 GALLON (3.785 L)

VEDCO

CAUTION: FLAMMABLE!

KEEP AWAY FROM FIRE OR FLAME

KEEP OUT OF REACH OF CHILDREN

For Animal Use Only

Scrub hands and arms with soap and water, rinse with water, then scrub with alcohol solution for disinfecting.

External solution for use as a topical antiseptic. May also be used for temporary relief of minor muscular aches or pain due to over-exertion and fatigue. Apply full strength directly to afflicted area, we thoroughly and massage briskly to stimulate circulation.

Store at controlled room temperature between 15° and 30°C (59°-86°F).

Rev. 6-99

TAKE TIME OBSERVE LABEL DIRECTIONS

Distributed by:
Vedco, Inc.

St. Joseph, MO 64504

ACTIVE INGREDIENT:

Isopropyl Alcohol ................ 70%

INERT INGREDIENT:

Deionized Water ................. 30%
Total ................................. 100%

WARNING:

For external use only. If taken internally, serious gastric disturbance will result. Avoid contact with eyes. In case of eye contact, flush thoroughly with water. Call a physician.

First Aid: Induce vomiting or use stomach pump.

SAFE HANDLING WARNING

FLAMMABLE: Do not use near heat or open flame.

Lot No.

Exp. Date